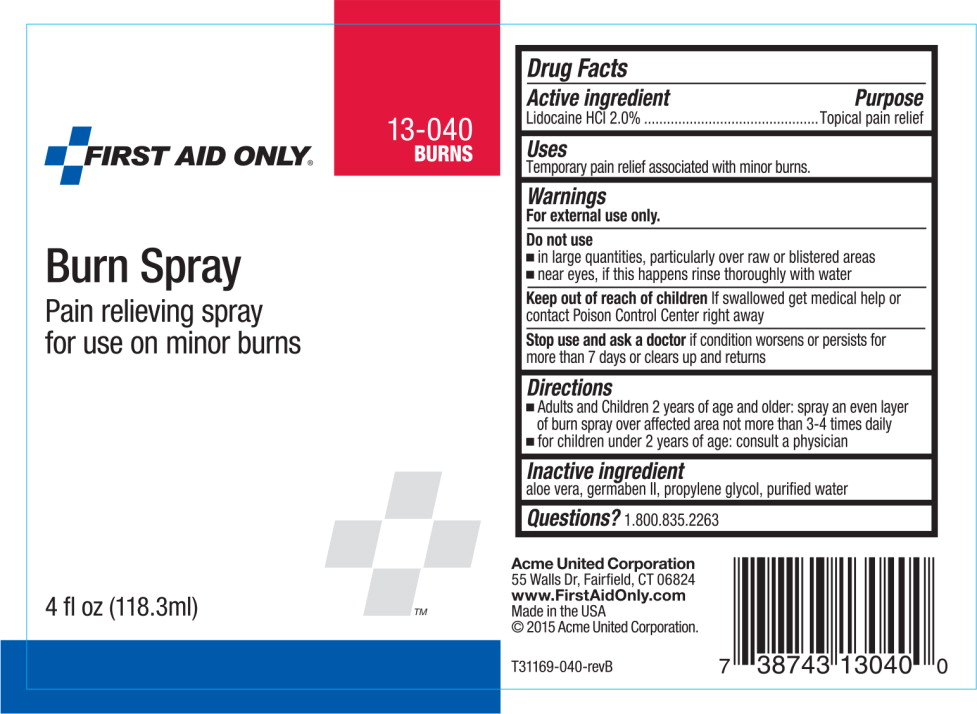 DRUG LABEL: Burn
NDC: 0924-0930 | Form: SPRAY
Manufacturer: Acme United Corp
Category: otc | Type: HUMAN OTC DRUG LABEL
Date: 20141006

ACTIVE INGREDIENTS: Lidocaine Hydrochloride 20 mg/1 L
INACTIVE INGREDIENTS: aloe vera leaf; propylene glycol; diazolidinyl urea; water

Drug Facts

Active ingredient

Lidocaine HCl 2.0%

Purpose

Topical pain relief

Uses

temporary pain relief associated with minor burns

Warnings

For external use only

Do not use

- in large quantities, particularly over raw or blistered areas
- near eyes, if this happens rinse thoroughly with water

Stop use and ask a doctor if condition worsens or persists for more than 7 days or clears up and returns

Keep out of reach of children. If swallowed get medical help or contact Poison Control Center right away

Directions

- adults and children 2 years of age and older: spray an even layer of burn spray over affected area not more than 3-4 times daily
- for children under 2 years of age: consult a physician

Inactive ingredients

aloe vera, germaben II, propylene glycol, purified water

Questions?

call 203-857-5361

Principal Display Panel - Bottle Label

13-040

BURNS

FIRST AID ONLY®

Burn Spray

Pain relieving spray
for use on minor burns

4 fl oz (118.3ml)